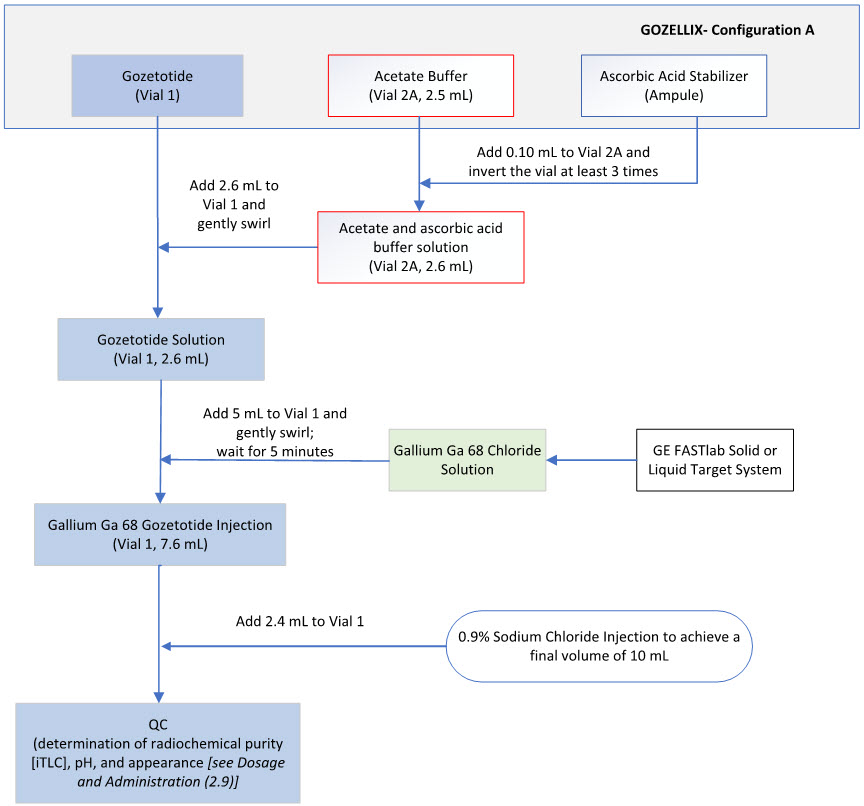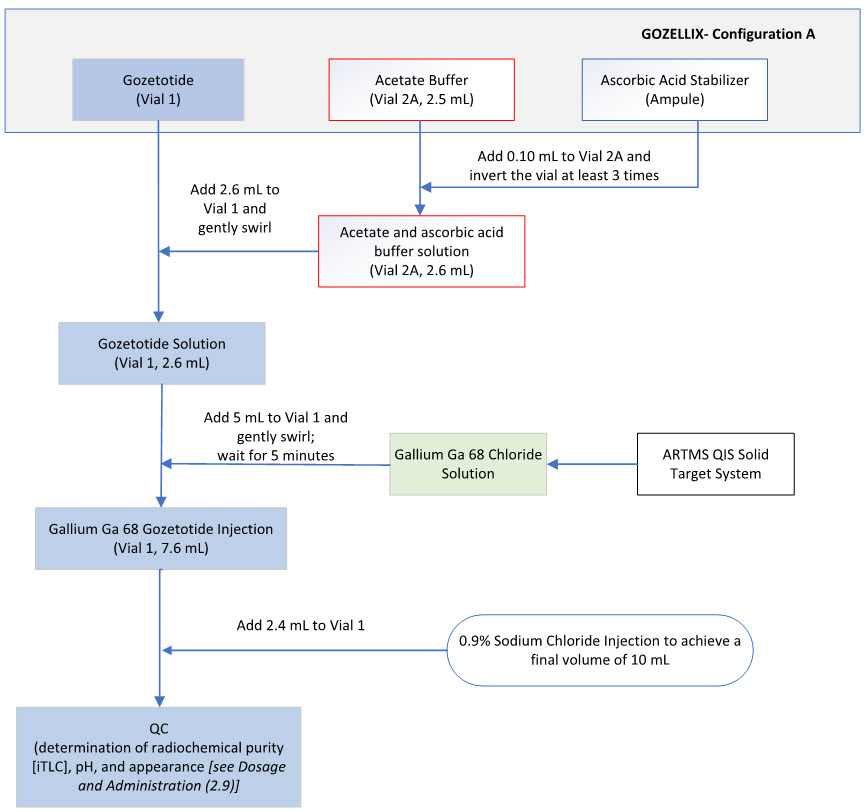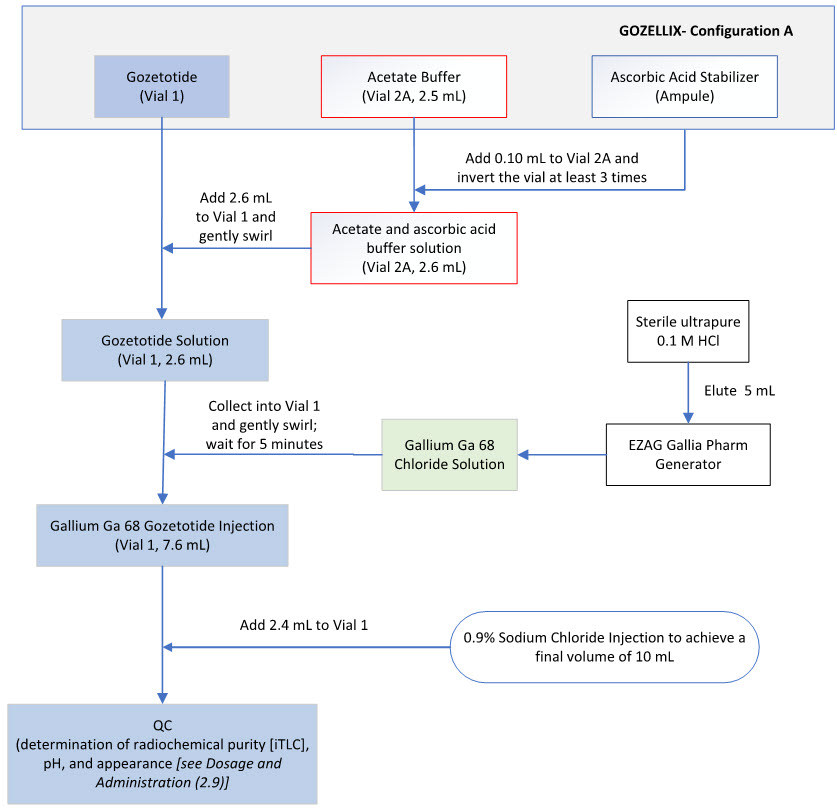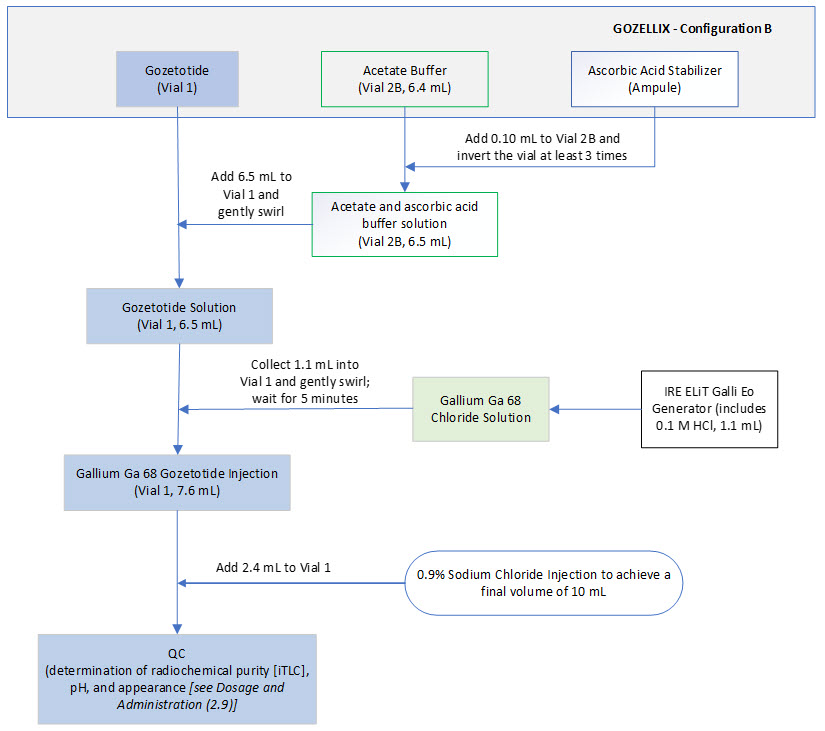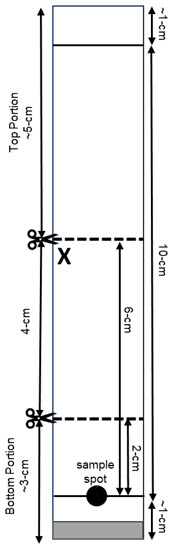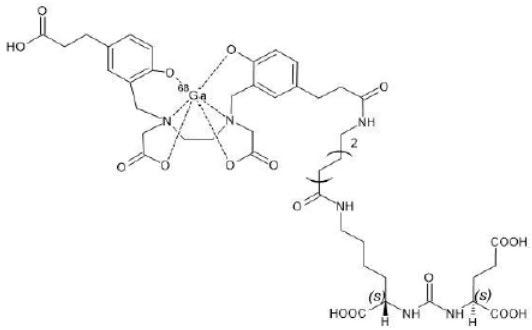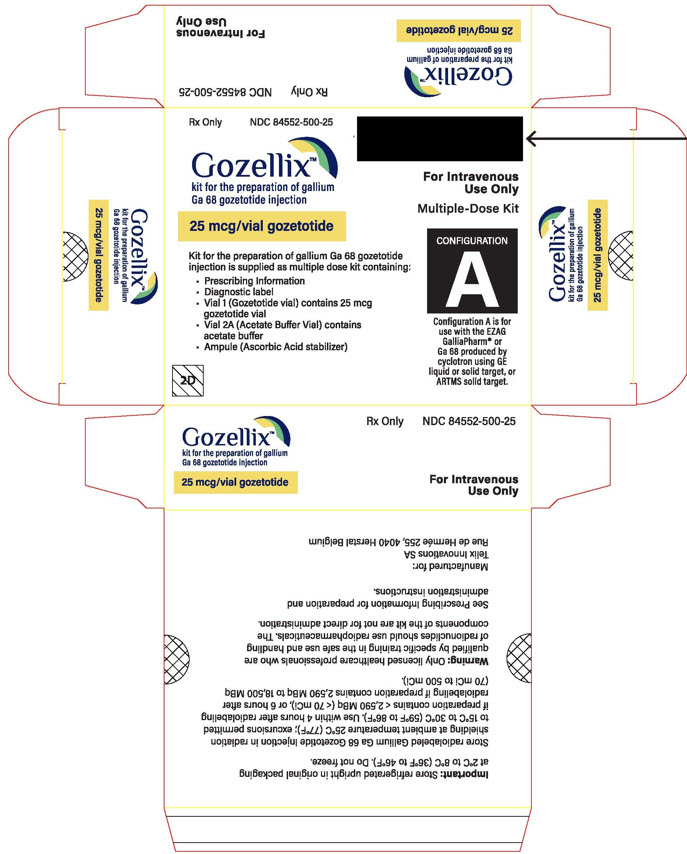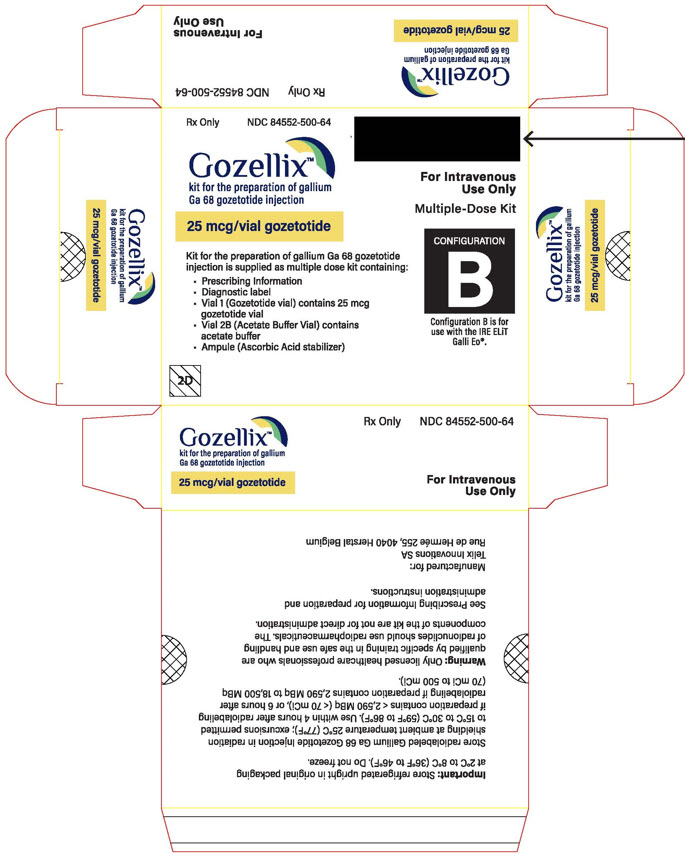 DRUG LABEL: Gozellix
NDC: 84552-500 | Form: KIT | Route: INTRAVENOUS
Manufacturer: Telix Innovations SA
Category: prescription | Type: HUMAN PRESCRIPTION DRUG LABEL
Date: 20250411

ACTIVE INGREDIENTS: GOZETOTIDE 25 mg/1 1
INACTIVE INGREDIENTS: DEMANNOSE 10 ug/1 1; SODIUM ACETATE ANHYDROUS 150 mg/2.5 mL; HYDROCHLORIC ACID; SODIUM ACETATE ANHYDROUS 150 mg/6.4 mL; HYDROCHLORIC ACID; ASCORBIC ACID 500 mg/2 mL; WATER; SODIUM METABISULFITE; SODIUM HYDROXIDE

HIGHLIGHTS OF PRESCRIBING INFORMATION

These highlights do not include all the information needed to use GOZELLIX safely and effectively. See full prescribing information for GOZELLIX.
GOZELLIX™ (kit for the preparation of gallium Ga 68 gozetotide injection), for intravenous use
Initial U.S. Approval: 2020

1 INDICATIONS AND USAGE

GOZELLIX, after radiolabeling with Ga 68, is a radioactive diagnostic agent indicated for positron emission tomography (PET) of prostate-specific membrane antigen (PSMA) positive lesions in men with prostate cancer:

- With suspected metastasis who are candidates for initial definitive therapy.
- With suspected recurrence based on elevated serum prostate-specific antigen (PSA) level. (1)

2 DOSAGE AND ADMINISTRATION

- Use appropriate aseptic technique and radiation safety handling measures in the manipulation and administration of Gallium Ga 68 Gozetotide Injection. (2.1)
- The recommended amount of radioactivity for adults is 111 MBq to 259 MBq (3 mCi to 7 mCi) as a bolus intravenous injection. (2.2)
- A diuretic expected to act within the uptake time period may be administered at the time of radiotracer injection. (2.2)
- Initiate imaging 50 minutes to 100 minutes after administration. The patient should void immediately prior to initiation of imaging. The scan should begin caudally and proceed cranially. (2.10)
- See full prescribing information for additional preparation, administration, imaging, and radiation dosimetry information. (2)

3 DOSAGE FORMS AND STRENGTHS

Kit for the preparation of Gallium Ga 68 Gozetotide Injection contains:

- Vial 1 (Gozetotide): 25 mcg gozetotide as a lyophilized powder in a multiple-dose vial
- Vial 2A (2.5 mL) or Vial 2B (6.4 mL) (Acetate Buffer): 150 mg of anhydrous sodium acetate as a sterile solution
  - Vial 2A in Configuration A for use with cyclotron-produced Ga 68 via GE FASTlab or ARTMS QIS, or EZAG generator
  - Vial 2B in Configuration B for use with IRE generator
- Ampule (Ascorbic Acid Stabilizer): 500 mg/2 mL (250 mg/mL) ascorbic acid (USP injection grade) as a sterile solution. (3)

After radiolabeling with Ga 68, Vial 1 contains up to 18,500 MBq (500 mCi) of Gallium Ga 68 Gozetotide Injection in 10 mL in a multiple-dose vial at calibration date and time.

4 CONTRAINDICATIONS

None (4)

5 WARNINGS AND PRECAUTIONS

- Risk for Misinterpretation: Gallium Ga 68 gozetotide uptake can be seen in a variety of tumor types and in non-malignant processes. Clinical correlation, which may include histopathological evaluation of the suspected prostate cancer site, is recommended. (5.1)
- Radiation Risks: Ensure safe handling to protect patients and health care providers from unintentional radiation exposure. (2.1, 5.2)
- Hypersensitivity Reactions to Sulfites: Ascorbic Acid Stabilizer contains sodium metabisulfite, a sulfite that may cause life-threatening hypersensitivity reactions including anaphylaxis. (5.3)

6 ADVERSE REACTIONS

The most commonly reported adverse reactions include nausea, diarrhea, and dizziness. (6)

To report SUSPECTED ADVERSE REACTIONS, contact Telix Pharmaceuticals (US) Inc. at 1-844-455-8638 or contact FDA at 1-800-FDA-1088 or www.fda.gov/medwatch.

FULL PRESCRIBING INFORMATION

1 INDICATIONS AND USAGE

GOZELLIX, after radiolabeling with Ga 68, is indicated for positron emission tomography (PET) of prostate-specific membrane antigen (PSMA) positive lesions in men with prostate cancer:

- With suspected metastasis who are candidates for initial definitive therapy.
- With suspected recurrence based on elevated serum prostate-specific antigen (PSA) level.

2 DOSAGE AND ADMINISTRATION

2.1 Radiation Safety - Drug Handling

After radiolabeling of GOZELLIX, the vial contains Gallium Ga 68 Gozetotide Injection. Handle Gallium Ga 68 Gozetotide Injection with appropriate safety measures to minimize radiation exposure [see Warnings and Precautions (5.2)] . Use waterproof gloves, effective radiation shielding, and other appropriate safety measures when preparing and handling Gallium Ga 68 Gozetotide Injection.

Radiopharmaceuticals should be used by or under the control of healthcare providers who are qualified by specific training and experience in the safe use and handling of radionuclides, and whose experience and training have been approved by the appropriate governmental agency authorized to license the use of radionuclides.

2.2 Recommended Dosage and Administration Instructions

Recommended Dosage

In adults, the recommended amount of radioactivity to be administered for PET is 111 MBq to 259 MBq (3 mCi to 7 mCi) administered as an intravenous bolus injection.

Administration

- Use aseptic technique and radiation shielding when withdrawing and administering Gallium Ga 68 Gozetotide Injection.
- Calculate the necessary volume to administer based on calibration time and required dose.
- Inspect Gallium Ga 68 Gozetotide Injection visually for particulate matter and discoloration before administration. Only use solutions that are clear, colorless to slightly yellow, and without visible particles.
- Assay the final dose in a dose calibrator immediately before administration to the patient.
- After injection of Gallium Ga 68 Gozetotide Injection, administer an intravenous flush of sterile 0.9% Sodium Chloride Injection to ensure full delivery of the dose.
- Dispose of any unused drug in a safe manner in compliance with applicable regulations.
- Unless contraindicated, a diuretic expected to act within the uptake time period may be administered at the time of radiotracer injection to potentially decrease artifact from radiotracer accumulation in the urinary bladder and ureters.

2.3 Patient Preparation

Instruct patients to drink a sufficient amount of water to ensure adequate hydration prior to administration of Gallium Ga 68 Gozetotide Injection and to continue to drink and void frequently following administration to reduce radiation exposure, particularly during the first hour after administration [see Warnings and Precautions (5.2)] .

2.4 General Instructions for Drug Preparation

Ga 68 Sources and GOZELLIX Carton Configurations

GOZELLIX is supplied as a kit in two different carton configurations, A or B, for preparation of Gallium Ga 68 Gozetotide Injection with eluate from different Ga 68 sources. See Table 1for GOZELLIX carton configurations to be used with different Ga 68 sources.

Table 1. Ga 68 Sources and GOZELLIX Carton Configuration
Ga 68 Source | GOZELLIX Carton Configuration to be Used
Cyclotron-produced via GE FASTlab | A
Cyclotron-produced via Alternative Radioisotope Technologies for Medical Science (ARTMS) QUANTM Irradiation System (QIS) | A
Eckert & Ziegler (EZAG) GalliaPharm Germanium 68/Gallium 68 (Ge 68/Ga 68) generator | A
IRE ELiT Galli Eo Ge 68/Ga 68 generator | B

The Ge 68/Ga 68 generators and cyclotron are not supplied with GOZELLIX. Follow the instructions for use provided by the Ge 68/Ga 68 generator or cyclotron manufacturer.

Components of GOZELLIX consist of Vial 1 (Gozetotide), Vial 2A or Vial 2B (Acetate Buffer), and an Ampule (Ascorbic Acid Stabilizer) [see How Supplied/Storage and Handling (16)] .

General Instructions

1. Follow aseptic techniques in all drug preparation and handling.
2. Use suitable shielding to reduce radiation exposure.
3. Wear waterproof gloves.
4. Place a "radioactive" label on Vial 1 (Gozetotide) with product name, lot number and date.
5. Remove the vial cap from Vial 1 (Gozetotide) and Vial 2A or Vial 2B (Acetate Buffer).
6. Swab the top of each vial and the outside of the ampule with alcohol to disinfect the surface and allow the top of each vial to dry.
7. Use the shortest possible needle for the transfer of the Gallium Ga 68 Chloride solution to minimize any potential metallic contamination. The needle should be clean and dilute acid resistant.
8. Use only plastic syringes for preparation and administration. Do notuse syringes with rubber plungers.
9. Prior to use of any vial, confirm the correct vial by a visual check of the vial label.
10. Prepare the acetate buffer by adding 0.10 mL ascorbic acid stabilizer according to the instruction below before proceeding with the specific procedure depending on Ga 68 source.
11. Follow the specific preparation procedure dependent on Ga 68 source [see Dosage and Administration (2.5, 2.6, 2.7, 2.8)] .

Procedure for Addition of Ascorbic Acid Stabilizer to Acetate Buffer

1. Safely open the ascorbic acid stabilizer ampule.
2. Using an appropriately sized syringe (e.g., 0.5 mL syringe) fitted with a 5 micron 18 G × 1 1/2 inch sterile filter needle or equivalent, withdraw the solution of ascorbic acid, through the filter needle.
  NOTE: The syringe must contain at least 0.10 mL of ascorbic acid stabilizer solution that can then be dispensed. The operator must account for the dead volume of the syringe and filter needle.
3. Remove the filter needle from the syringe and fit a sterile needle to the syringe containing the ascorbic acid.
4. Dispense 0.10 mL of the ascorbic acid stabilizer solution from the syringe into the acetate buffer vial (Vial 2A or Vial 2B).
5. After removal of the syringe from the vial, mix the contents by inverting the vial at least three times.

2.5 Preparation with Cyclotron-Produced Ga 68 via GE FASTlab Solid or Liquid Target System

Collection of Gallium Ga 68 Chloride Solution

After purification by the FASTlab, the Gallium Ga 68 Chloride solution is passed through a sterile filter and into the cassette product vial automatically by the FASTlab.

When Ga 68 is cyclotron-produced, test for Ga 66 and Ga 67 (with specification of ≤2% combined total) when a new lot of Zn 68 is introduced for manufacturing.

Radiolabeling Procedure

1. Use GOZELLIX "Configuration A" with cyclotron-produced Ga 68 via GE FASTlab Solid or Liquid Target System.
2. A schematic diagram for the preparation is provided in Figure 1.
3. Prepare the acetate buffer (Vial 2A) with ascorbic acid stabilizer as outlined in the procedure above [see Dosage and Administration (2.4)] .
4. Pierce Vial 1 (Gozetotide) with a sterile needle connected to a 0.2 micron sterile vented filter to maintain atmospheric pressure within the vial during the reconstitution process.
5. Insert a sterile syringe with a needle into Vial 2A containing the acetate and ascorbic acid buffer solution and draw up 2.6 mL of the solution.
6. Aseptically transfer the acetate and ascorbic acid buffer solution in the syringe into Vial 1 (Gozetotide).
7. Gently swirl Vial 1 to ensure the product is thoroughly dissolved in the buffer.
8. Aseptically transfer the 5 mL of Gallium Ga 68 Chloride solution made using the GE FASTlab Solid or Liquid Target System into Vial 1 (Gozetotide).
9. Remove the sterile vent filter.
10. Gently swirl Vial 1 to ensure the product is thoroughly mixed.
11. Wait for 5 minutes for radiolabeling to take place at room temperature (25°C (77°F); excursions permitted to 15°C to 30°C (59°F to 86°F)).
12. Assay the whole vial containing the Gallium Ga 68 Gozetotide Injection for total radioactivity using a dose calibrator, calculate the radioactivity concentration, and record the result.
13. Dilute the Gallium Ga 68 Gozetotide Injection with 2.4 mL of 0.9% Sodium Chloride Injection to a final volume of 10 mL.
14. Perform the quality control of Gallium Ga 68 Gozetotide Injection according to the recommended methods [see Dosage and Administration (2.9)] .
15. Prior to use, visually inspect the solution behind a shielded screen for radioprotection purposes. Only use solutions that are clear without visible particles.
16. Keep the vial containing the Gallium Ga 68 Gozetotide Injection upright in a radioprotective shield container at room temperature until use.
17. The final volume of the Gallium Ga 68 Gozetotide Injection is 10 mL after dilution with 0.9% Sodium Chloride Injection.
18. Use within 4 hours if preparation contains less than 2,590 MBq (70 mCi) or within 6 hours if preparation contains 2,590 MBq to 18,500 MBq (70 mCi to 500 mCi) .

Figure 1: Drug Preparation with Cyclotron-Produced Ga 68 via GE FASTlab Solid or Liquid Target System

2.6 Preparation with Cyclotron-Produced Ga 68 via ARTMS QIS Solid Target System

Collection of Gallium Ga 68 Chloride Solution

After purification by the ARTMS QIS, the Gallium Ga 68 Chloride solution is passed through a sterile filter and into the cassette product vial automatically by the ARTMS QIS.

When Ga 68 is cyclotron-produced, test for Ga 66 and Ga 67 (with specification of ≤2% combined total) when a new lot of Zn 68 is introduced for manufacturing.

Radiolabeling Procedure

1. Use GOZELLIX "Configuration A" with cyclotron-produced Ga 68 via ARTMS QIS Solid Target System.
2. A schematic diagram for the preparation is provided in Figure 2.
3. Prepare the acetate buffer (Vial 2A) with ascorbic acid stabilizer as outlined in the procedure above [see Dosage and Administration (2.4)] .
4. Pierce Vial 1 (Gozetotide) with a sterile needle connected to a 0.2 micron sterile vented filter to maintain atmospheric pressure within the vial during the reconstitution process.
5. Insert a sterile syringe with a needle into Vial 2A containing the acetate and ascorbic acid buffer solution and draw up 2.6 mL of the solution.
6. Aseptically transfer the acetate and ascorbic acid buffer solution in the syringe into Vial 1 (Gozetotide).
7. Gently swirl Vial 1 to ensure the product is thoroughly dissolved in the buffer.
8. Aseptically transfer the 5 mL of Gallium Ga 68 Chloride solution made using the ARTMS QIS Solid Target System into Vial 1 (Gozetotide).
9. Remove the sterile vent filter.
10. Gently swirl Vial 1 to ensure the product is thoroughly mixed.
11. Wait for 5 minutes for radiolabeling to take place at room temperature (25°C (77°F)); excursions permitted to 15°C to 30°C (59°F to 86°F)).
12. Assay the whole vial containing the Gallium Ga 68 Gozetotide Injection for total radioactivity using a dose calibrator, calculate the radioactivity concentration, and record the result.
13. Dilute the Gallium Ga 68 Gozetotide Injection with 2.4 mL of 0.9% Sodium Chloride Injection to a final volume of 10 mL.
14. Perform the quality control of Gallium Ga 68 Gozetotide Injection according to the recommended methods [see Dosage and Administration (2.9)] .
15. Prior to use, visually inspect the solution behind a shielded screen for radioprotection purposes. Only use solutions that are clear without visible particles.
16. Keep the vial containing the Gallium Ga 68 Gozetotide Injection upright in a radioprotective shield container at room temperature until use.
17. The final volume of the Gallium Ga 68 Gozetotide Injection is 10 mL after dilution with 0.9% Sodium Chloride Injection.
18. Use within 4 hours if preparation contains less than 2,590 MBq (70 mCi) or within 6 hours if preparation contains 2,590 MBq to 18,500 MBq (70 mCi to 500 mCi).

Figure 2: Drug Preparation with Cyclotron-Produced Ga 68 via ARTMS QIS Solid Target System

2.7 Preparation with EZAG GalliaPharm Generator

Follow the generator manufacturers' instructions for generator preparation, controls, and continuous routine elution.

Radiolabeling Procedure

1. Use GOZELLIX "Configuration A" with an EZAG GalliaPharm generator.
2. A schematic diagram for the preparation is provided in Figure 3.
3. Prepare the acetate buffer vial (Vial 2A) with ascorbic acid stabilizer as outlined in the procedure above [see Dosage and Administration (2.4)] .
4. Pierce Vial 1 (Gozetotide) with a sterile needle connected to a 0.2 micron sterile vented filter to maintain atmospheric pressure within the vial during the reconstitution process.
5. Insert a sterile syringe with a needle into Vial 2A containing the acetate and ascorbic acid buffer solution and draw up 2.6 mL of the solution.
6. Aseptically transfer the acetate and ascorbic acid buffer solution in the syringe into Vial 1 (Gozetotide).
7. Gently swirl Vial 1 to ensure the product is thoroughly dissolved in the buffer.
8. Prepare a syringe containing 5 mL of sterile ultrapure 0.1 M HCl provided with the GalliaPharm generator for elution.
9. Connect the male luer of the outlet line of the GalliaPharm generator to a sterile needle.
10. Connect Vial 1 containing the dissolved gozetotide solution directly to the outlet line of the GalliaPharm generator by pushing the needle through the rubber septum and place the vial in a radiation shielded container.
11. Ensure the vent needle and needle to the generator outlet are pulled up as far as possible to not contact the solution in the vial.
12. Elute the generator directly with the 5 mL 0.1 M HCl from step 8 into Vial 1 according to the instructions for use of the GalliaPharm generator that are supplied by EZAG.
13. At the end of the elution, disconnect the generator from Vial 1 by removing the needle from the rubber septum and remove the sterile vent filter.
14. Gently swirl the vial to ensure the product is thoroughly mixed.
15. Wait for 5 minutes for radiolabeling to take place at room temperature (25°C (77°F); excursions permitted to 15°C to 30°C (59°F to 86°F)).
16. Assay the whole vial containing the Gallium Ga 68 Gozetotide Injection for total radioactivity using a dose calibrator, calculate the radioactivity concentration, and record the result.
17. Dilute the Gallium Ga 68 Gozetotide Injection with 2.4 mL of 0.9% Sodium Chloride Injection to a final volume of 10 mL.
18. Perform the quality control of Gallium Ga 68 Gozetotide Injection according to the recommended methods [see Dosage and Administration (2.9)] .
19. Prior to use, visually inspect the solution behind a shielded screen for radioprotection purposes. Only use solutions that are clear without visible particles.
20. Keep the vial containing the Gallium Ga 68 Gozetotide Injection upright in a radioprotective shield container at room temperature until use.
21. The final volume of the Gallium Ga 68 Gozetotide Injection is 10 mL after dilution with 0.9% Sodium Chloride Injection.
22. Use within 4 hours if preparation contains less than 2,590 MBq (70 mCi) or within 6 hours if preparation contains 2,590 MBq to 18,500 MBq (70 mCi to 500 mCi).

Figure 3: Preparation with EZAG GalliaPharm Generator

2.8 Preparation with IRE ELiT Galli Eo Generator

Follow the generator manufacturers' instructions for generator preparation, controls, and continuous routine elution.

Radiolabeling Procedure

1. Use GOZELLIX "Configuration B" with an IRE EliT Galli Eo generator.
2. A schematic diagram for the preparation is provided in Figure 4.
3. Prepare the acetate buffer vial (Vial 2B) with ascorbic acid stabilizer as outlined in the procedure above [see Dosage and Administration (2.4)] .
4. Pierce Vial 1 (Gozetotide) with a sterile needle connected to a 0.2 micron sterile vented filter to maintain atmospheric pressure within the vial during the reconstitution process.
5. Insert a sterile syringe with a needle into Vial 2B containing the acetate and ascorbic acid buffer solution and draw up 6.5 mL of the solution.
6. Aseptically transfer the acetate and ascorbic acid buffer solution in the syringe into Vial 1 (Gozetotide).
7. Gently swirl Vial 1 to ensure the product is thoroughly dissolved in the buffer.
8. Remove the 0.2 micron sterile vented filter from Vial 1.
9. Connect the male luer of the outlet line of the Galli Eo generator to a sterile needle.
10. Connect Vial 1 containing the dissolved gozetotide solution directly to the outlet line of the Galli Eo generator by pushing the needle through the vial's septum.
11. Ensure the needle to the generator outlet is pulled up as far as possible to not contact the solution in the vial.
12. Elute 1.1 mL from the generator directly into Vial 1 (Gozetotide) according to the instructions for use of the Galli Eo generator that are supplied by IRE that describe elution into a non-evacuated vial.
13. At the end of the elution, disconnect the generator from Vial 1 by removing the needle from the rubber septum.
14. Gently swirl Vial 1 to ensure the product is thoroughly mixed.
15. Wait for 5 minutes for radiolabeling to take place at room temperature (25°C (77°F); excursions permitted to 15°C to 30°C (59°F to 86°F)).
16. Assay the whole vial containing the Gallium 68 Gozetotide Injection for total radioactivity using a dose calibrator, calculate the radioactivity concentration, and record the result.
17. Dilute the Gallium Ga 68 Gozetotide Injection with 2.4 mL of 0.9% Sodium Chloride Injection to a final volume of 10 mL.
18. Perform the quality control of Gallium Ga 68 Gozetotide Injection according to the recommended methods [see Dosage and Administration (2.9)] .
19. Prior to use, visually inspect the solution behind a shielded screen for radioprotection purposes. Only use solutions that are clear without visible particles.
20. Keep the vial containing the Gallium Ga 68 Gozetotide Injection upright in a radioprotective shield container at room temperature until use.
21. The final volume of the Gallium Ga 68 Gozetotide Injection is 10 mL after dilution with 0.9% Sodium Chloride Injection.
22. Use within 4 hours if preparation contains less than 2,590 MBq (70 mCi) or within 6 hours if preparation contains 2,590 MBq to 18,500 MBq (70 mCi to 500 mCi).

Figure 4: Preparation with IRE ELiT Galli Eo Generator

2.9 Specifications and Quality Control

Perform the quality controls in Table 2 behind a lead glass shield for radioprotection purposes.

Table 2: Specifications for Gallium Ga 68 Gozetotide Injection
Test | Analytical method | Acceptance criteria
Appearance | Visual examination | Colorless to slightly yellow solution Free from visible particles
pH | pH-meter or pH-strips | 4.0 to 5.0
Radiochemical purity | Instant thin-layer chromatography, silica gel (iTLC SG); See methods below
- Content of gallium Ga 68 gozetotide - Content of free and colloidal Ga 68 | Instant thin-layer chromatography, silica gel (iTLC SG); See methods below | ≥95% ≤5%

Procedure for instant Thin Layer Chromatography (iTLC)

1. Pour ammonium acetate 1 M/methanol (1/1 v/v) solution to a depth of 3 mm to 4 mm in the developing chamber, cover the chamber and allow it to equilibrate.
2. Prepare an iTLC strip that is 12 cm in length approximately 2.5 cm in width.
3. Using a pencil and ruler, carefully draw a solid line at least 1 cm from the bottom of the iTLC strip.
4. Using a pencil and ruler, carefully draw a solid line 10 cm above the pencil line drawn in Step 3.
5. Using a pencil and ruler, draw a dotted line 2 cm above the solid line at the bottom of the iTLC strip.
6. Using a pencil and ruler, draw a second dotted line 6 cm above the solid line at the bottom of the iTLC strip. Mark the section below this line with an "X". See Figure 5for an example of how to mark the iTLC strip.
7. Apply a drop of gallium Ga 68 gozetotide solution into the center of the solid line at 1 cm from the bottom of the TLC plate.
8. Place the iTLC strip into the development chamber, with the bottom of the iTLC strip containing drop of gallium Ga 68 gozetotide into the solution at the bottom of the developing chamber. Ensure that the bottom of the iTLC strip sits in the liquid in the chamber, but that the liquid does not touch the drop of gallium Ga 68 gozetotide.
9. Allow the iTLC strip to develop in the covered chamber over a distance of 10 cm from the point of application (until the solvent reaches the solid line near the top of the iTLC strip).
10. Remove the iTLC strip. Allow the plate to dry before proceeding with analysis using one of the methods described below.

Perform one of the following:

Radiochemical Purity Analysis Using Cutting Technique

1. Cut the iTLC strip into 3 parts by cutting horizontally at the dotted line 2 cm above the solid line at the bottom of the iTLC strip and the dotted line 6 cm above the solid line at the bottom of the iTLC strip. See Figure 5for where to cut the iTLC strip.
2. This cutting will result in the following 3 portions:
  1. A 3 cm portion containing the Origin and free/colloidal Ga 68 species (Bottom Portion)
  2. A 4 cm portion marked with an "X" containing no sample (this portion is NOT measured)
  3. A 5 cm portion containing the solvent front and gallium Ga 68 gozetotide (Top Portion)
3. Using a dose calibrator or gamma spectrometer, measure and record the radioactivity in the 3 cm portion of the cut TLC plate that contains the Origin and free/colloidal Ga 68 species (Bottom Portion).
4. Using a dose calibrator or gamma spectrometer, measure and record the radioactivity in the 5 cm portion containing the solvent front and gallium Ga 68 gozetotide (Top Portion).
5. Calculate the quantity (in percent) of gallium Ga 68 gozetotide in the solution using the formula:

Radiochemical Purity (%)
 | = | Counts Top Portion | × 100
 | = | Counts from Top Portion + Counts from Bottom Portion | × 100

Figure 5: iTLC Strip Preparation and Cutting Points for the Cutting Technique

Radiochemical Purity Analysis Using Scanning Technique

1. Scan the iTLC strip with a radiometric iTLC scanner.
2. Calculate the quantity (in percent) of gallium Ga 68 gozetotide in the solution by integration of the peaks on the chromatogram.
3. The retention factor (Rf) specifications are:
  - Free and colloidal Ga 68 species, Rf = 0 to 0.1,
  - Gallium Ga 68 gozetotide, Rf = 0.6 to 1.

2.10 Image Acquisition

Position the patient supine with arms above the head. Begin PET scanning 50 minutes to 100 minutes after the intravenous administration of Gallium Ga 68 Gozetotide Injection. Patients should void immediately prior to image acquisition and image acquisition should begin at the proximal thighs and proceed cranially to the skull base or skull vertex. Adapt imaging technique according to the equipment used and patient characteristics in order to obtain the best image quality possible.

2.11 Image Interpretation

Gallium Ga 68 gozetotide binds to PSMA. Based on the intensity of the signals, PET images obtained using gallium Ga 68 gozetotide indicate the presence of PSMA in tissues. Lesions should be considered suspicious if uptake is greater than physiologic uptake in that tissue or greater than adjacent background if no physiologic uptake is expected. Tumors that do not express PSMA will not be visualized. Increased uptake in tumors is not specific for prostate cancer [see Warnings and Precautions (5.1)] .

2.12 Radiation Dosimetry

Estimated radiation absorbed doses per injected activity for organs and tissues of adult male patients following an intravenous bolus of Gallium Ga 68 Gozetotide Injection are shown in Table 3.

The effective radiation dose resulting from the administration of the maximum recommended activity of 259 MBq (7 mCi) is about 4.4 mSv. The radiation doses for this administered activity to the critical organs, which are the kidneys, urinary bladder, and spleen, are 96.2 mGy, 25.4 mGy, and 16.8 mGy, respectively.

These radiation doses are for Gallium Ga 68 Gozetotide Injection alone. If CT or a transmission source are used for attenuation correction, the radiation dose will increase by an amount that varies by technique.

Table 3: Estimated Radiation Absorbed Dose per Injected Activity in Selected Organs and Tissues of Adults after Intravenous Administration of Gallium Ga 68 Gozetotide Injection
Organ | Absorbed dose (mGy/MBq)
Organ | Mean | SD
Adrenals | 0.0156 | 0.0014
Brain | 0.0104 | 0.0011
Breasts | 0.0103 | 0.0011
Gallbladder | 0.0157 | 0.0012
Lower Colon | 0.0134 | 0.0009
Small Intestine | 0.014 | 0.002
Stomach | 0.0129 | 0.0008
Heart | 0.012 | 0.0009
Kidneys | 0.3714 | 0.0922
Liver | 0.0409 | 0.0076
Lungs | 0.0111 | 0.0007
Muscle | 0.0103 | 0.0003
Pancreas | 0.0147 | 0.0009
Red Marrow | 0.0114 | 0.0016
Skin | 0.0091 | 0.0003
Spleen | 0.065 | 0.018
Testes | 0.0111 | 0.0006
Thymus | 0.0105 | 0.0006
Thyroid | 0.0104 | 0.0006
Urinary Bladder | 0.0982 | 0.0286
Total Body | 0.0143 | 0.0013
Effective Dose (mSv/MBq) | 0.0169 | 0.0015

3 DOSAGE FORMS AND STRENGTHS

Kit for the preparation of Gallium Ga 68 Gozetotide Injection contains:

- Vial 1 (Gozetotide): 25 mcg of gozetotide as a white to off-white lyophilized powder in a multiple-dose vial
- Vial 2A (2.5 mL) or Vial 2B (6.4 mL) (Acetate Buffer): 150 mg anhydrous sodium acetate as a sterile clear colorless solution
  - Vial 2A in Configuration A for use with cyclotron-produced Ga 68 via GE FASTlab or ARTMS QIS, or EZAG Gallia Pharm generator
  - Vial 2B in Configuration B for use with IRE EliT Galli Eo generator
- Ampule (Ascorbic Acid Stabilizer): 500 mg/2 mL (250 mg/mL) of ascorbic acid (USP injection grade) as a sterile clear colorless solution

After radiolabeling with Ga 68, Vial 1 contains up to 18,500 MBq (500 mCi) of Gallium Ga 68 Gozetotide Injection in 10 mL at calibration date and time as a clear, colorless to slightly yellow solution in a multiple-dose vial.

4 CONTRAINDICATIONS

None

5 WARNINGS AND PRECAUTIONS

5.1 Risk for Misinterpretation

Image interpretation errors can occur with GOZELLIX PET. A negative image does not rule out the presence of prostate cancer and a positive image does not confirm the presence of prostate cancer. Gallium Ga 68 gozetotide uptake is not specific for prostate cancer and may occur with other types of cancer as well as non-malignant processes such as Paget's disease, fibrous dysplasia, and osteophytosis. The performance of GOZELLIX for imaging of biochemically recurrent prostate cancer seems to be affected by serum PSA levels and by site of disease. The performance of GOZELLIX for imaging of metastatic pelvic lymph nodes prior to initial definitive therapy seems to be affected by Gleason score [see Clinical Studies (14.1, 14.2)] .

Clinical correlation, which may include histopathological evaluation of the suspected prostate cancer site, is recommended.

5.2 Radiation Risks

Gallium Ga 68 gozetotide contributes to a patient's overall long-term cumulative radiation exposure. Long-term cumulative radiation exposure is associated with an increased risk for cancer. Ensure safe handling to minimize radiation exposure to the patient and health care providers. Advise patients to hydrate before and after administration and to void frequently after administration [see Dosage and Administration (2.1, 2.3)] .

5.3 Hypersensitivity Reactions to Sulfites

Ascorbic Acid Stabilizer contains sodium metabisulfite, a sulfite that may cause allergic-type reactions including anaphylactic symptoms and life-threatening or less severe asthmatic episodes in certain susceptible people. The overall prevalence of sulfite sensitivity in the general population is unknown and probably low. Sulfite sensitivity is seen more frequently in asthmatic than in non-asthmatic people.

6 ADVERSE REACTIONS

Clinical Trials Experience

Because clinical trials are conducted under widely varying conditions, adverse reaction rates observed in the clinical trials of a drug cannot be directly compared to rates in the clinical trials of another drug and may not reflect the rates observed in practice.

The safety of GOZELLIX has been established based on two prospective studies of another formulation of gallium Ga 68 gozetotide in patients with prostate cancer [see Clinical Studies (14.1, 14.2)] . Below is a display of the adverse reactions in these studies.

The safety of gallium Ga 68 gozetotide was evaluated in 960 patients in the PSMA-PreRP and PSMA-BCR studies, each receiving one dose of gallium Ga 68 gozetotide. The average injected activity was 188.7 ± 40.7 MBq (5.1 ± 1.1 mCi) [see Clinical Studies (14.1, 14.2)] . The most commonly reported adverse reactions were nausea, diarrhea, and dizziness, occurring at a rate of <1%.

7 DRUG INTERACTIONS

Androgen deprivation therapy and other therapies targeting the androgen pathway

Androgen deprivation therapy (ADT) and other therapies targeting the androgen pathway, such as androgen receptor antagonists, can result in changes in uptake of gallium Ga 68 gozetotide in prostate cancer. The effect of these therapies on performance of gallium Ga 68 gozetotide PET has not been established.

8 USE IN SPECIFIC POPULATIONS

8.1 Pregnancy

Risk Summary

GOZELLIX is not indicated for use in females. There are no available data with gallium Ga 68 gozetotide injection use in pregnant women to evaluate for a drug-associated risk of major birth defects, miscarriage, or adverse maternal or fetal outcomes. All radiopharmaceuticals, including GOZELLIX, have the potential to cause fetal harm depending on the fetal stage of development and the magnitude of the radiation dose. Animal reproduction studies have not been conducted with gallium Ga 68 gozetotide.

8.2 Lactation

Risk Summary

GOZELLIX is not indicated for use in females. There are no data on the presence of gallium Ga 68 gozetotide in human milk, the effect on the breastfed infant, or the effect on milk production.

8.4 Pediatric Use

The safety and effectiveness of gallium Ga 68 gozetotide in pediatric patients have not been established.

8.5 Geriatric Use

The efficacy of gallium Ga 68 gozetotide PET in geriatric patients with prostate cancer is based on data from two prospective studies [see Clinical Studies (14.1, 14.2)].

Of the total number of subjects in the PSMA-PreRP and PSMA-BCR studies, 691 of 960 (72%) patients were 65 years of age and older while 195 (20%) were 75 years of age and older.

The efficacy and safety profiles of gallium Ga 68 gozetotide appear similar in younger adult and geriatric patients with prostate cancer and other reported clinical experience has not identified differences in responses between the elderly and younger adult patients.

10 OVERDOSAGE

In the event of an overdose of gallium Ga68 gozetotide, reduce the radiation absorbed dose to the patient where possible by increasing the elimination of the drug from the body using hydration and frequent bladder voiding. A diuretic might also be considered. If possible, an estimate of the radiation effective dose given to the patient should be made.

11 DESCRIPTION

11.1 Drug Characteristics

GOZELLIX (kit for the preparation of gallium Ga 68 gozetotide injection), after radiolabeling with Ga 68, is a radioactive diagnostic agent for intravenous use. Gozetotide is also known as PSMA-11.

Gallium Ga 68 gozetotide is a radioconjugate composed of a human prostate specific membrane antigen (PSMA)-targeting ligand peptide conjugated via the acyclic radiometal chelator, N,N'-bis [2-hydroxy-5-(carboxyethyl)benzyl] ethylenediamine-N,N'-diacetic acid (HBED-CC) to the radioisotope Ga 68. The amino acid sequence of the gozetotide peptide is Glu-NH-CO-NH-Lys(Ahx), (Ahx = 6-aminohexanoic acid). Gallium Ga 68 gozetotide has a molecular weight of 1011.9 g/mol and its chemical structure is shown in Figure 6.

Figure 6: Chemical Structure of Gallium Ga 68 Gozetotide

Kit Characteristics

GOZELLIX is supplied as a kit which contains the non-radioactive ingredients needed to produce Gallium Ga 68 Gozetotide Injection. There are two configurations, A or B, available to allow preparation of Gallium Ga 68 Gozetotide Injection using Ga 68 from different generator or cyclotron sources. Each configuration consists of gozetotide (Vial 1), acetate buffer (Vial 2A or Vial 2B), and ascorbic acid stabilizer (Ampule).

- Vial 1 (Gozetotide): Each vial contains 25 mcg gozetotide and 10 mcg D-mannose.
- Vial 2A (Acetate Buffer): Each vial contains 150 mg anhydrous sodium acetate in 2.5 mL of 0.292 M hydrochloric acid.
- Vial 2B (Acetate Buffer): Each vial contains 150 mg anhydrous sodium acetate in 6.4 mL of 0.175 M hydrochloric acid.
- Ampule (Ascorbic Acid Stabilizer): Each ampule contains 500 mg of ascorbic acid (USP injection grade), 3 mg sodium metabisulfite, sodium hydroxide for pH adjustment, and water for injection in a volume of 2 mL.

The prepared Gallium Ga 68 Gozetotide Injection is a sterile, pyrogen free, clear, colorless to slightly yellow, buffered solution containing up to 18,500 MBq (500 mCi) of gallium Ga 68 gozetotide in 10 mL with a pH between 4.0 to 5.0.

11.2 Nuclear Physical Characteristics

Gallium-68 (Ga 68) decays with a half-life of 68 minutes to stable zinc-68. Table 4, Table 5, and Table 6 display the principal radiation emission data, radiation attenuation by lead shielding, and physical decay of Ga 68.

Table 4: Principal Radiation Emission Data (>1%) for Ga 68
Radiation/ Emission | % Disintegration | Mean Energy (MeV)
beta+ | 88% | 0.8360
beta+ | 1.1% | 0.3526
gamma | 178% | 0.5110
gamma | 3.0% | 1.0770
X-ray | 2.8% | 0.0086
X-ray | 1.4% | 0.0086

Table 5: Radiation Attenuation of 511 keV Photons by Lead (Pb) Shielding
Shield Thickness (Pb) mm | Coefficient of Attenuation
6 | 0.5
12 | 0.25
17 | 0.1
34 | 0.01
51 | 0.001

Table 6: Physical Decay Chart for Ga 68
Minutes | Fraction Remaining
0 | 1
15 | 0.858
30 | 0.736
60 | 0.541
90 | 0.398
120 | 0.293
180 | 0.158
360 | 0.025

12 CLINICAL PHARMACOLOGY

12.1 Mechanism of Action

Gallium Ga 68 gozetotide binds to PSMA. It binds to cells that express PSMA, including malignant prostate cancer cells, which usually overexpress PSMA. Gallium-68 is a β+ emitting radionuclide that allows positron emission tomography.

12.2 Pharmacodynamics

The relationship between gallium Ga 68 gozetotide plasma concentrations and successful imaging was not explored in clinical trials.

12.3 Pharmacokinetics

Distribution

Intravenously injected gallium Ga 68 gozetotide is cleared from the blood and is accumulated preferentially in the liver (15%), kidneys (7%), spleen (2%), and salivary glands (0.5%). Gallium Ga 68 gozetotide uptake is also seen in the adrenals and prostate. There is no uptake in the cerebral cortex or in the heart, and usually lung uptake is low.

Elimination

A total of 14% of the injected dose is excreted in urine in the first 2 hours post-injection.

13 NONCLINICAL TOXICOLOGY

13.1 Carcinogenesis, Mutagenesis, Impairment of Fertility

No long-term animal studies were performed to evaluate the carcinogenicity potential of gallium Ga 68 gozetotide.

14 CLINICAL STUDIES

14.1 Imaging Prior to Initial Definitive Therapy

The efficacy of GOZELLIX for PET of PSMA-positive lesions in men with prostate cancer with suspected metastasis who are candidates for initial definitive therapy has been established based on a study of another formulation of gallium Ga 68 gozetotide. Below is a display of the results of the prospective, open label study PSMA-PreRP (NCT03368547 and NCT02919111).

This two-center study enrolled 325 patients with biopsy-proven prostate cancer who were considered candidates for prostatectomy and pelvic lymph node dissection. All enrolled patients met at least one of the following criteria: serum prostate-specific antigen (PSA) of at least 10 ng/mL, tumor stage cT2b or greater, or Gleason score greater than 6. Each patient received a single gallium Ga 68 gozetotide PET/CT or PET/MR from mid-thigh to skull base.

A total of 123 patients (38%) proceeded to standard-of-care prostatectomy and template pelvic lymph node dissection and had sufficient histopathology data for evaluation (evaluable patients). Three members of a pool of six central readers independently interpreted each PET scan for the presence of abnormal gallium Ga 68 gozetotide uptake in pelvic lymph nodes located in the common iliac, external iliac, internal iliac, and obturator subregions bilaterally as well as in any other pelvic location. The readers were blinded to all clinical information except for the history of prostate cancer prior to definitive treatment. Extrapelvic sites and the prostate gland itself were not analyzed in this study. For each patient, gallium Ga 68 gozetotide PET results and reference standard histopathology obtained from dissected pelvic lymph nodes were compared by region (left hemipelvis, right hemipelvis, and other).

For the 123 evaluable patients, the mean age was 65 years (range 45 to 76 years), and 89% were white. The median serum PSA was 11.8 ng/mL. The summed Gleason score was 7 for 44%, 8 for 20%, and 9 for 31% of the patients, with the remainder of the patients having Gleason scores of 6 or 10.

Table 7 compares majority PET reads to pelvic lymph node histopathology results at the patient-level with region matching, such that at least one true positive region defines a true positive patient. As shown, approximately 24% of subjects studied were found to have pelvic nodal metastases based on histopathology (95% confidence interval: 17%, 32%).

Table 7: Patient-Level Performance of Gallium Ga 68 Gozetotide PET for Detection of Pelvic Lymph Node Metastasis [with region matching where at least one true positive region defines a true positive patient] in the PSMA-PreRP Study (n=123)
 |  | Histopathology |  | Predictive value [PPV: positive predictive value, NPV: negative predictive value] (95% CI)
 |  | Positive | Negative | Predictive value [PPV: positive predictive value, NPV: negative predictive value] (95% CI)
PET scan | Positive | 14 | 9 | PPV 61% (41%, 81%)
PET scan | Negative | 16 | 84 | NPV 84% (79%, 91%)
Total |  | 30 | 93
Diagnostic performance (95% CI) |  | Sensitivity 47% (29%, 65%) | Specificity 90% (84%, 96%)

Among the pool of six readers, sensitivity ranged from 36% to 60%, specificity from 83% to 96%, positive predictive value from 38% to 80%, and negative predictive value from 80% to 88%. In an exploratory subgroup analysis based on summed Gleason score, there was a numerical trend toward more true positives in patients with Gleason score of 8 or higher compared to those with Gleason score of 7 or lower.

An exploratory analysis was performed to estimate the sensitivity and specificity for pelvic nodal metastasis detection in all scanned patients, including the patients who were lacking histopathology reference standard. An imputation method was used based on patient-specific factors. This exploratory analysis resulted in an imputed sensitivity of 47%, with a 95% confidence interval ranging from 38% to 55%, and an imputed specificity of 74%, with a 95% confidence interval ranging from 68% to 80% for all patients imaged with gallium Ga 68 gozetotide PET.

14.2 Imaging Prior to Suspected Recurrence Therapy

The efficacy of GOZELLIX for PET of PSMA-positive lesions in men with prostate cancer with suspected recurrence based on elevated serum PSA level has been established based on a study of another formulation of gallium Ga 68 gozetotide. Below is a display of the results of the prospective, open label study PSMA-BCR (NCT02940262 and NCT02918357).

This two-center study enrolled 635 patients with biochemical evidence of recurrent prostate cancer after definitive therapy, defined by serum PSA of >0.2 ng/mL more than 6 weeks after prostatectomy or by an increase in serum PSA of at least 2 ng/mL above nadir after definitive radiotherapy. All patients received a single gallium Ga 68 gozetotide PET/CT or PET/MR from mid-thigh to skull base. Three members of a pool of nine independent central readers evaluated each scan for the presence and regional location (20 subregions grouped into four regions) of abnormal gallium Ga 68 gozetotide uptake suggestive of recurrent prostate cancer. The readers were blinded to all clinical information other than type of primary therapy and most recent serum PSA level.

A total of 469 patients (74%) had at least one positive region detected by gallium Ga 68 gozetotide PET majority read. The distribution of gallium Ga 68 gozetotide PET positive regions was 34% bone, 25% prostate bed, 25% pelvic lymph node, and 17% extrapelvic soft tissue. Two hundred and ten patients had composite reference standard information collected in a PET positive region (evaluable patients), consisting of at least one of the following: histopathology, imaging (bone scintigraphy, CT, or MRI) acquired at baseline or within 12 months after gallium Ga 68 gozetotide PET, or serial serum PSA.

Composite reference standard information for gallium Ga 68 gozetotide PET negative regions was not systematically collected in this study.

In the 210 evaluable patients, the mean age was 70 years (range 49 to 88 years) and 82% were 65 years of age or older. White patients made up 90% of the group. The median serum PSA was 3.6 ng/mL. Prior treatment included radical prostatectomy in 64% and radiotherapy in 73%.

Of the 210 evaluable patients, 192 patients (91%) were found to be true positive in one or more regions against the composite reference standard (95% confidence interval: 88%, 95%). Among the pool of nine readers used in the study, the proportion of patients who were true positive in one or more regions ranged from 82% to 97%. The prostate bed had the lowest proportion of true positive results at the region-level (76% versus 96% for non-prostate regions).

An exploratory analysis was also performed in which gallium Ga 68 gozetotide PET positive patients who lacked reference standard information were imputed using an estimated likelihood that at least one location-matched PET positive lesion was reference standard positive based on patient-specific factors. In this exploratory analysis, 340 of 475 patients (72%) were imputed as true positive in one or more regions (95% confidence interval: 68%, 76%).

In another exploratory analysis using the same imputation approach for PET positive patients who lacked reference standard information, 340 of 635 patients (54%) were correctly detected as true positive (95% confidence interval: 50%, 57%) among all BCR patients who received a PET scan, whether it was read as positive or negative.

The likelihood of identifying a gallium Ga 68 gozetotide PET positive lesion in this study increased with higher serum PSA level. Table 8 shows the patient-level gallium Ga 68 gozetotide PET results stratified by serum PSA level. The mean time between PSA measurement and PET scan was 40 days with a range of 0 to 367 days. Percent PET positivity was calculated as the proportion of patients with a positive gallium Ga 68 gozetotide PET out of all patients scanned. Percent PET positivity includes patients determined to be either true positive or false positive as well as those in whom such determination was not made due to the absence of composite reference standard data.

Table 8: Patient-Level Gallium Ga 68 Gozetotide PET Results and Percent PET Positivity Stratified by Serum PSA Level in the PSMA-BCR Study (n=628) [7 patients were excluded from this table due to protocol deviations]
PSA (ng/mL) | PET positive patients |  |  |  | PET negative patients | Percent PET positivity [Percent PET positivity = PET positive patients/total patients scanned] (95% CI)
PSA (ng/mL) | Total | TP [TP: true positive, FP: false positive] | FP | Without reference standard | PET negative patients | Percent PET positivity [Percent PET positivity = PET positive patients/total patients scanned] (95% CI)
PSA (ng/mL) | Total | With reference standard |  | Without reference standard | PET negative patients | Percent PET positivity [Percent PET positivity = PET positive patients/total patients scanned] (95% CI)
<0.5 | 48 | 11 | 1 | 36 | 87 | 36% (27%, 44%)
<0.5 | 48 | 12 |  | 36 | 87 | 36% (27%, 44%)
≥0.5 and <1 | 44 | 15 | 3 | 26 | 35 | 56% (45%, 67%)
≥0.5 and <1 | 44 | 18 |  | 26 | 35 | 56% (45%, 67%)
≥1 and <2 | 71 | 29 | 1 | 41 | 15 | 83% (75%, 91%)
≥1 and <2 | 71 | 30 |  | 41 | 15 | 83% (75%, 91%)
≥2 | 299 | 137 | 13 | 149 | 29 | 91% (88%, 94%)
≥2 | 299 | 150 |  | 149 | 29 | 91% (88%, 94%)
Total | 462 | 192 | 18 | 252 | 166 | 74% (70%, 77%)
Total | 462 | 210 |  | 252 | 166 | 74% (70%, 77%)

16 HOW SUPPLIED/STORAGE AND HANDLING

How Supplied

GOZELLIX (kit for the preparation of gallium Ga 68 gozetotide injection) is available in two different configurations.

GOZELLIX Configuration "A" (NDC 84552-500-25), intended for use with Ga 68 produced from a cyclotron and purified via GE FASTlab or ARTMS QIS, or an Eckert & Ziegler GalliaPharm Ge 68/Ga 68 generator, contains:

- Vial 1 (Gozetotide): 25 mcg gozetotide as a sterile white to off-white lyophilized powder in a multiple-dose vial with a blue flip-off cap (NDC 84552-501-25)
- Vial 2A (Acetate Buffer): 150 mg/2.5 mL of anhydrous sodium acetate as a sterile clear colorless solution in a vial with a red flip off cap (NDC 84552-502-25)
- Ampule (Ascorbic Acid Stabilizer): 500 mg/2 mL (250 mg/mL) of ascorbic acid (USP injection grade) as a sterile clear colorless solution in a glass ampule (NDC 84552-504-25)

GOZELLIX Configuration "B" (NDC 84552-500-64), intended for use with Ga 68 produced from an IRE Galli Eo Ge 68/Ga 68 generator, contains:

- Vial 1 (Gozetotide): 25 mcg gozetotide as a sterile white to off-white lyophilized powder in a multiple-dose vial with a blue flip-off cap (NDC 84552-501-25)
- Vial 2B (Acetate Buffer): 150 mg/6.4 mL of anhydrous sodium acetate as a sterile clear colorless solution in a vial with a green flip off cap (NDC 84552-503-64)
- Ampule (Ascorbic Acid Stabilizer): 500 mg/2 mL (250 mg/mL) of ascorbic acid (USP injection grade) as a sterile clear colorless solution in a glass ampule (NDC 84552-504-25)

The radionuclide is not part of the kit. Before radiolabeling with Ga 68, the contents of this kit are not radioactive.

Storage and Handling

Store GOZELLIX refrigerated upright in the original packaging at 2° to 8°C (36° to 46°F). Do not freeze.

After radiolabeling, keep Gallium Ga 68 Gozetotide Injection upright with appropriate shielding to protect from radiation at room temperature (25°C (77°F); excursions permitted to 15°C to 30°C (59°F to 86°F)). Use Gallium Ga 68 Gozetotide Injection within the time frames described in Table 9 below.

Table 9: Shelf Life Per Activity of Gallium Ga 68 Gozetotide Injection
Activity | Shelf Life
Less than 2,590 MBq (70 mCi) | 4 hours
2,590 MBq to 18,500 MBq (70 mCi to 500 mCi) | 6 hours

Dispose of the product in accordance with all federal, state, and local laws and institutional requirements.

This preparation is approved for use by persons under license by the Nuclear Regulatory Commission or the relevant regulatory authority of an Agreement State.

17 PATIENT COUNSELING INFORMATION

Adequate Hydration

Instruct patients to drink a sufficient amount of water to ensure adequate hydration before their PET study and urge them to drink and urinate as often as possible during the first hours following the administration of Gallium Ga 68 Gozetotide Injection, in order to reduce radiation exposure [see Dosage and Administration (2.3)and Warnings and Precautions (5.2)] .

Manufactured for:
Telix Innovations SA
rue de Hermée 255 à 4040 Herstal, Belgium

For optional information on GOZELLIX, see www.gozellix.com.

GOZELLIX is a registered trademark of Telix Pharmaceuticals Limited
Copyright © 2025 Telix Innovations SA
All rights reserved.

PRINCIPAL DISPLAY PANEL - Kit Carton - Configuration A

Rx Only

NDC 84552-500-25

Gozellix™
kit for the preparation of gallium
Ga 68 gozetotide injection

25 mcg/vial gozetotide

Kit for the preparation of gallium Ga 68 gozetotide
injection is supplied as multiple dose kit containing:

- Prescribing Information
- Diagnostic label
- Vial 1 (Gozetotide vial) contains 25 mcg
  gozetotide vial
- Vial 2A (Acetate Buffer Vial) contains
  acetate buffer
- Ampule (Ascorbic Acid stabilizer)

2D

For Intravenous
Use Only

Multiple-Dose Kit

CONFIGURATION
A

Configuration A is for
use with the EZAG
GalliaPharm®or
Ga 68 produced by
cyclotron using GE
liquid or solid target, or
ARTMS solid target.

PRINCIPAL DISPLAY PANEL - Kit Carton - Configuration B

Rx Only

NDC 84552-500-64

Gozellix™
kit for the preparation of gallium
Ga 68 gozetotide injection

25 mcg/vial gozetotide

Kit for the preparation of gallium Ga 68 gozetotide
injection is supplied as multiple dose kit containing:

- Prescribing Information
- Diagnostic label
- Vial 1 (Gozetotide vial) contains 25 mcg
  gozetotide vial
- Vial 2B (Acetate Buffer Vial) contains
  acetate buffer
- Ampule (Ascorbic Acid stabilizer)

2D

For Intravenous
Use Only

Multiple-Dose Kit

CONFIGURATION
B

Configuration B is for
use with the IRE ELiT
Galli Eo®.